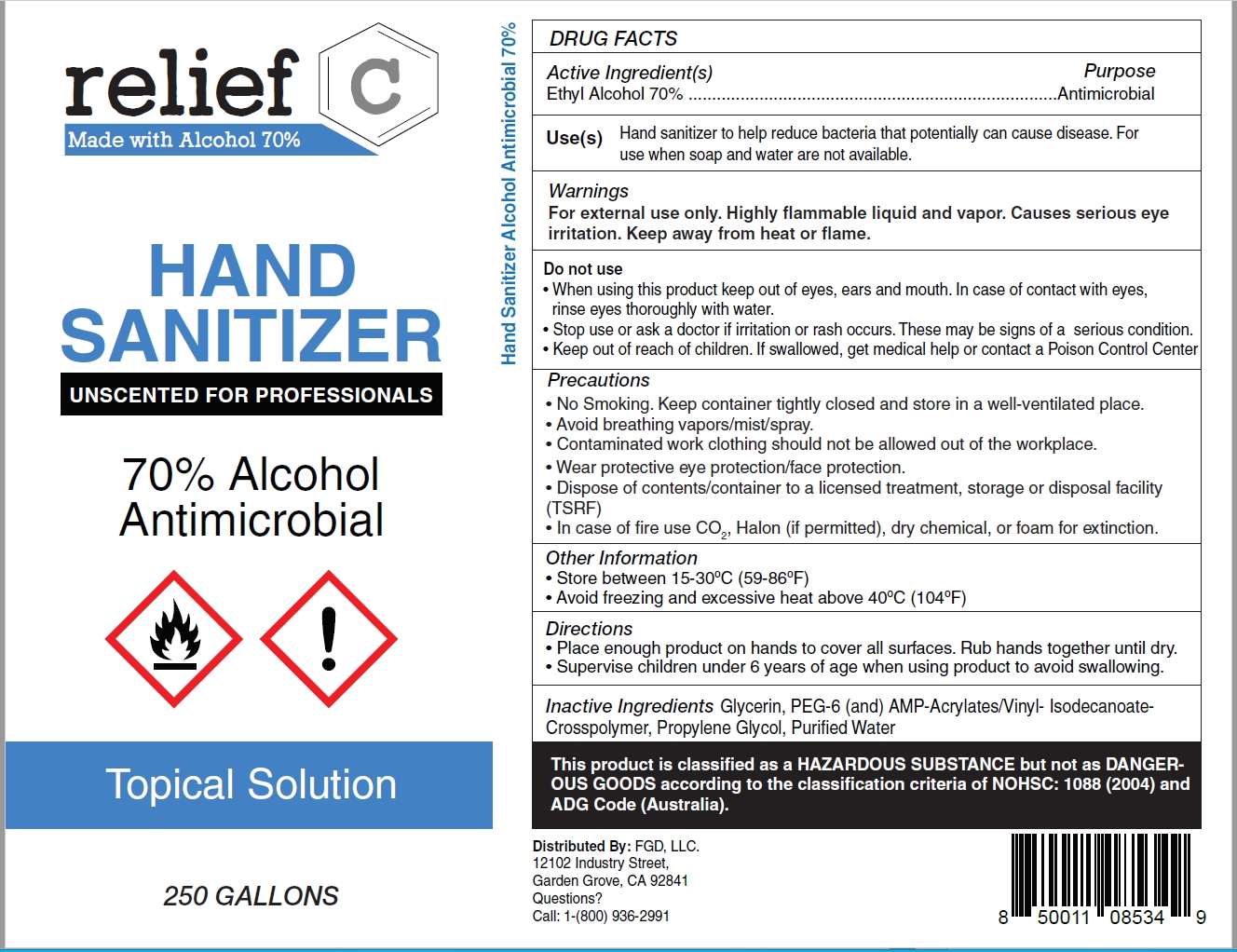 DRUG LABEL: Relief C Hand Sanitizer Unscented for Professionals
NDC: 73787-122 | Form: GEL
Manufacturer: FGD, LLC
Category: otc | Type: HUMAN OTC DRUG LABEL
Date: 20210106

ACTIVE INGREDIENTS: ALCOHOL 70 mL/100 mL
INACTIVE INGREDIENTS: WATER; POLYETHYLENE GLYCOL 300; ACRYLATES/VINYL ISODECANOATE CROSSPOLYMER (10000 MPA.S NEUTRALIZED AT 0.5%); GLYCERIN; PROPYLENE GLYCOL

Relief C Hand Sanitizer: Unscented for Professionals

Active ingredient

Ethyl Alcohol 70%

Purpose

Antimicrobial

Uses

Hand sanitizer to help reduce bacteria that potentially can cause disease. For use when soap and water are not available.

Warnings

For external use only. Highly flammable liquid and vapor. Causes serious eye irritation. Keep away from heat or flame.

Do Not Use

- If you are allergic to any of the ingredients
- In children less than 2 months of age
- On open skin wounds

When using this product keep out of eyes, ears and mouth.

In case of contact with eyes, rinse eyes thoroughly with water.

Stop use or ask a doctor if

Stop use and ask a doctor if irritation or rash occurs. These may be signs of a serious condition.

Keep out of reach of children

If swallowed, get medical help or contact a Poison Control Center (1-800-222-1222) right away.

PRECAUTIONS

- Keep away from heat/sparks/open flame/hot surfaces.
- No Smoking. Keep container tightly closed and store in a well-ventilated place.
- Avoid breathing vapors/mist/spray.
- Contaminated work clothing should not be allowed out of the workplace.
- Wear protective eye protection/face protection.
- Dispose of contents/container to a licensed treatment, storage or disposal facility (TSRF)
- If in eyes rinse continuously with water for several minutes. Remove contact lenses if present and easy to do – continue rinsing.
- In case of fire use CO2, Halon (if permitted), dry chemical, or foam for extinction.

Directions

- Place enough product on hands to cover all surfaces. Rub hands together until dry.
- Supervise children under 6 years of age when using this product to avoid swallowing.

Other Information

- Store between 15-30^0C (59-86^0F)
- Avoid freezing and excessive heat above 40^0C (104^0F)

Inactive ingredients

Carbapol 20, glycerin, proylene glycol, water